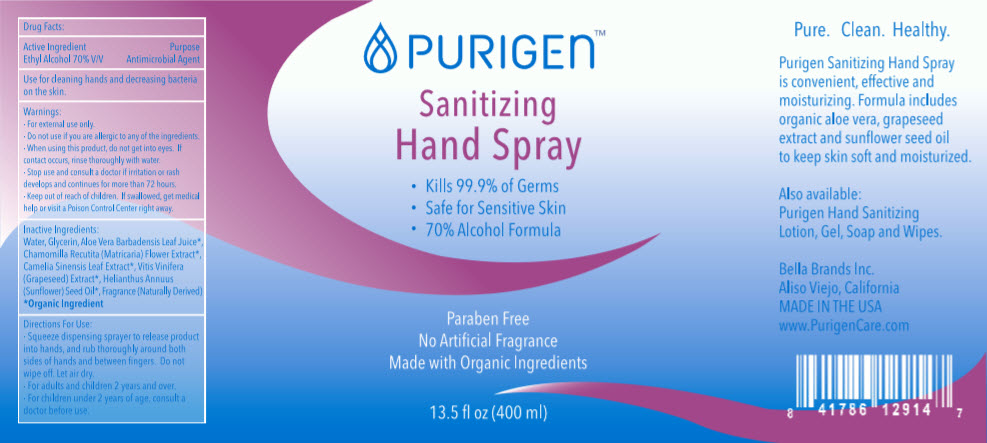 DRUG LABEL: Sanitizing Hand
NDC: 80994-003 | Form: SPRAY
Manufacturer: BELLA BRANDS INC
Category: otc | Type: HUMAN OTC DRUG LABEL
Date: 20201118

ACTIVE INGREDIENTS: Alcohol 70 mL/100 mL
INACTIVE INGREDIENTS: Water; Glycerin; Chamomile; Green Tea Leaf; Vitis Vinifera Seed; Sunflower Oil

Sanitizing Hand

Drug Facts:

Active Ingredient

Ethyl Alcohol 70% V/V

Purpose

Antimicrobial Agent

Use

for cleaning hands and decreasing bacteria on the skin.

Warnings

- For external use only.

- Do not use if you are allergic to any of the ingredients.

- When using this product, do not get into eyes. If contact occurs, rinse thoroughly with water.

- Stop use and consult a doctor if irritation or rash develops and continues for more than 72 hours.

- Keep out of reach of children. If swallowed, get medical help or visit a Poison Control Center right away.

Inactive Ingredients

Water, Glycerin, Aloe Vera Barbadensis Leaf Juice [Organic Ingredient] , Chamomilla Recutita (Matricaria) Flower Extract, Camelia Sinensis Leaf Extract, Vitis Vinifera (Grapeseed) Extract, Helianthus Annuus (Sunflower) Seed Oil, Fragrance (Naturally Derived)

Directions For Use

- Squeeze dispensing sprayer to release product into hands, and rub thoroughly around both sides of hands and between fingers. Do not wipe off. Let air dry.

- For adults and children 2 years and over.

- For children under 2 years of age, consult a doctor before use.

PRINCIPAL DISPLAY PANEL - 400 ml Bottle Label

PURIGEN™

Sanitizing
Hand Spray

- Kills 99.9% of Germs
- Safe for Sensitive Skin
- 70% Alcohol Formula

Paraben Free
No Artificial Fragrance
Made with Organic Ingredients

13.5 fl oz (400 ml)